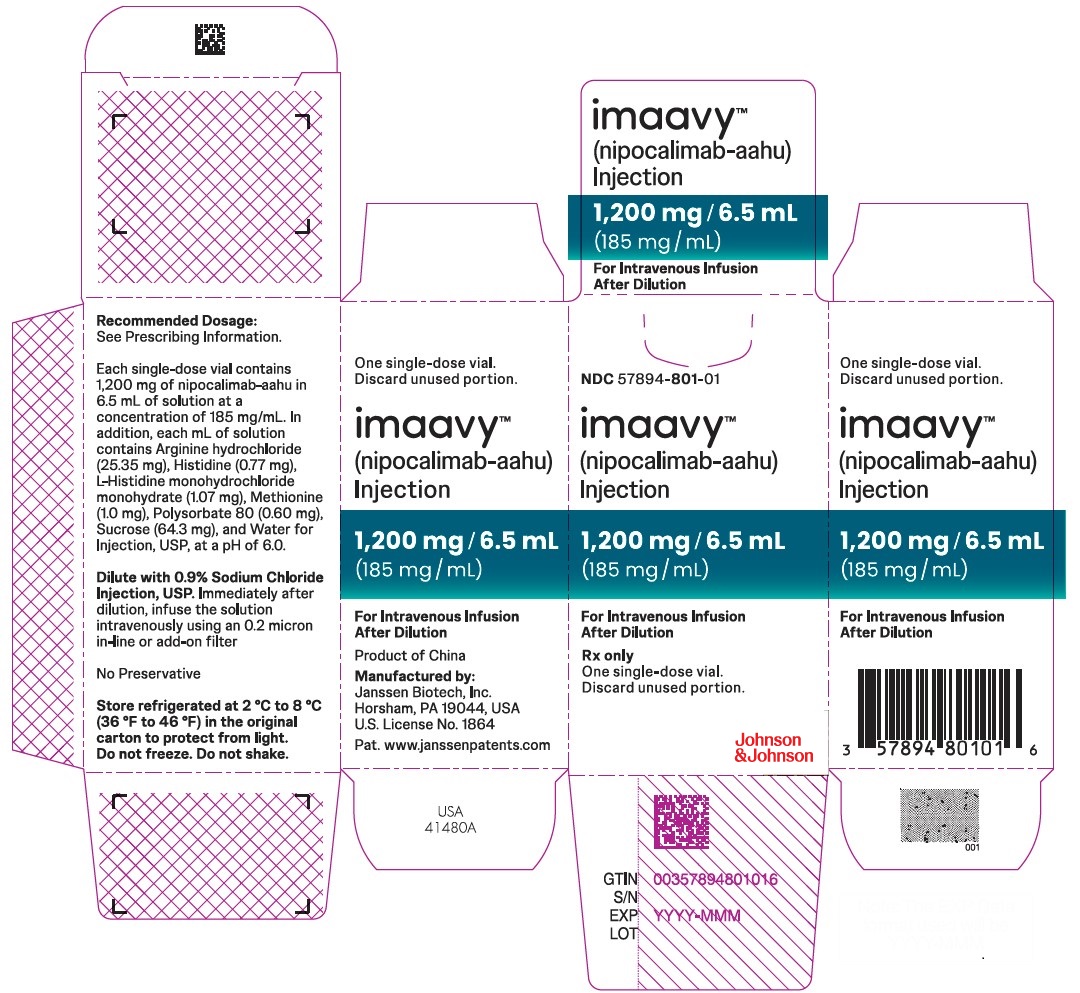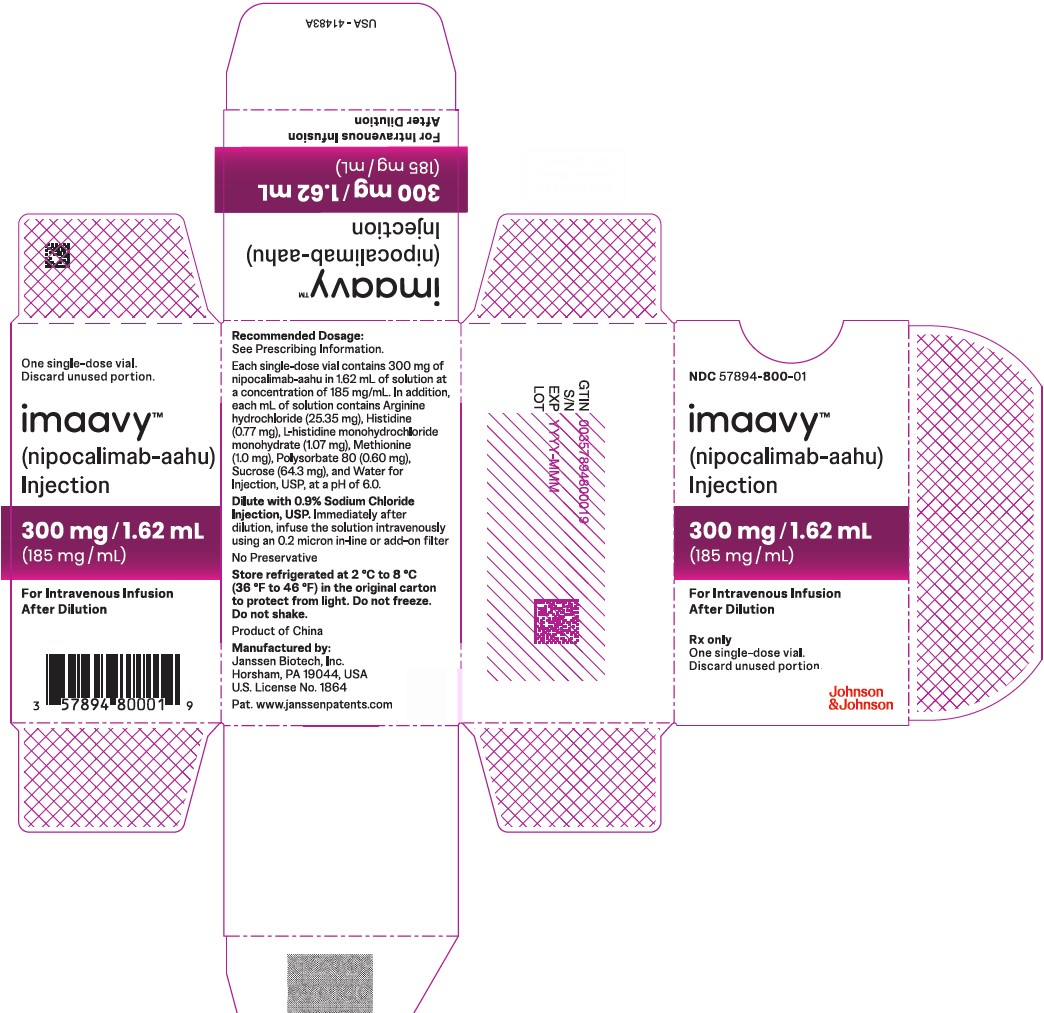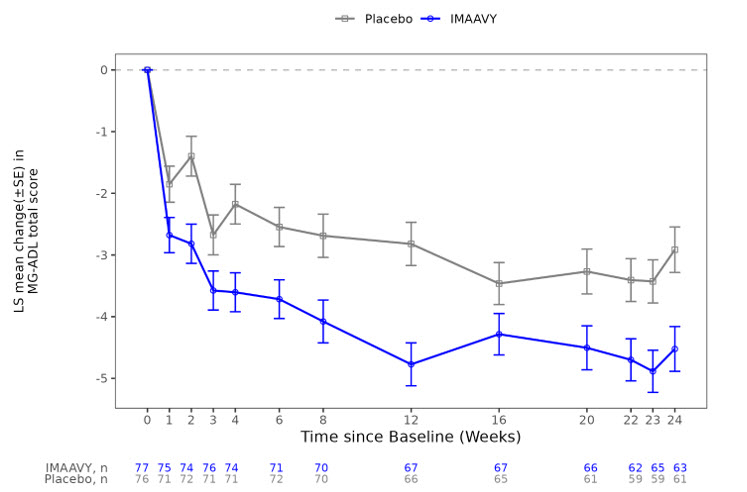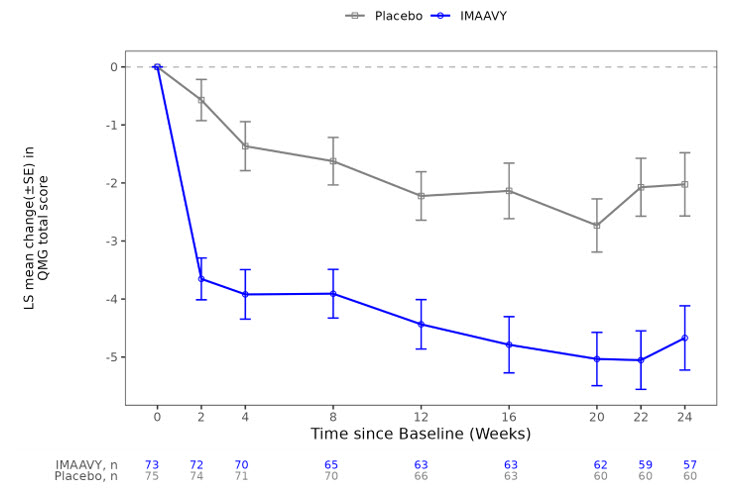 DRUG LABEL: IMAAVY
NDC: 57894-801 | Form: INJECTION, SOLUTION, CONCENTRATE
Manufacturer: Janssen Biotech, Inc.
Category: prescription | Type: HUMAN PRESCRIPTION DRUG LABEL
Date: 20250506

ACTIVE INGREDIENTS: NIPOCALIMAB 185 mg/1 mL
INACTIVE INGREDIENTS: ARGININE HYDROCHLORIDE; HISTIDINE; HISTIDINE MONOHYDROCHLORIDE MONOHYDRATE; METHIONINE; POLYSORBATE 80; SUCROSE; WATER

HIGHLIGHTS OF PRESCRIBING INFORMATION

These highlights do not include all the information needed to use IMAAVY safely and effectively. See full prescribing information for IMAAVY.
IMAAVY™ (nipocalimab-aahu) injection, for intravenous use
Initial U.S. Approval: 2025

1 INDICATIONS AND USAGE

IMAAVY is a neonatal Fc receptor blocker indicated for the treatment of generalized myasthenia gravis (gMG) in adult and pediatric patients 12 years of age and older who are anti-acetylcholine receptor (AChR) or anti-muscle-specific tyrosine kinase (MuSK) antibody positive. (1)

2 DOSAGE AND ADMINISTRATION

- See Full Prescribing Information for instructions on dosage, preparation, and administration. (2.1, 2.2, 2.3)
- Evaluate the need to administer age-appropriate vaccines according to immunization guidelines before initiation of IMAAVY. (2.1)
- Administer via intravenous infusion only. (2.2)
- The recommended initial dosage is 30 mg/kg once via intravenous infusion over at least 30 minutes. Two weeks after the initial dosage, administer a maintenance dosage of 15 mg/kg via intravenous infusion over at least 15 minutes, and continue every two weeks thereafter. (2.2)
- Must be diluted with 0.9% sodium chloride injection prior to administration. (2.3)
- Administer as an intravenous infusion via a 0.2 micron in-line or add-on filter. (2.3)

3 DOSAGE FORMS AND STRENGTHS

- Injection: 300 mg/1.62 mL (185 mg/mL) in a single-dose vial (3)
- Injection: 1,200 mg/6.5 mL (185 mg/mL) in a single-dose vial (3)

4 CONTRAINDICATIONS

IMAAVY is contraindicated in patients with a history of serious hypersensitivity reaction to nipocalimab or to any of the excipients in IMAAVY. (4)

5 WARNINGS AND PRECAUTIONS

- Infections: Delay administration of IMAAVY to patients with an active infection. Monitor for signs and symptoms of infection in patients treated with IMAAVY. If serious infection occurs, administer appropriate treatment and consider withholding IMAAVY until the infection has resolved. (5.1)
- Hypersensitivity Reactions: Angioedema, anaphylaxis, rash, urticaria, and eczema have occurred in patients treated with IMAAVY. If a hypersensitivity reaction occurs, discontinue the infusion and institute appropriate therapy. (5.2)
- Infusion-Related Reactions: If a severe infusion-related reaction occurs, discontinue the infusion and initiate appropriate therapy; consider the risks and benefits of readministering. If a mild to moderate infusion-related reaction occurs, may rechallenge with close clinical observation, slower infusion rates, and pre-medication. (5.3)

6 ADVERSE REACTIONS

The most common adverse reactions (≥10%) in patients with gMG treated with IMAAVY were respiratory tract infections, peripheral edema, and muscle spasms. (6.1)

To report SUSPECTED ADVERSE REACTIONS, contact Janssen Biotech, Inc. at 1-800-526-7736 or FDA at 1-800-FDA-1088 or www.fda.gov/medwatch.

7 DRUG INTERACTIONS

Closely monitor for reduced effectiveness of medications that bind to the human neonatal Fc receptor. When concomitant long-term use of such medications is essential for patient care, consider discontinuing IMAAVY and using alternative therapies. (7)

FULL PRESCRIBING INFORMATION

1 INDICATIONS AND USAGE

IMAAVY is indicated for the treatment of generalized myasthenia gravis (gMG) in adult and pediatric patients 12 years of age and older who are anti-acetylcholine receptor (AChR) or anti-muscle-specific tyrosine kinase (MuSK) antibody positive.

2 DOSAGE AND ADMINISTRATION

2.1 Recommended Vaccination

Evaluate the need to administer age-appropriate vaccines according to immunization guidelines before initiation of IMAAVY. Because IMAAVY causes transient reduction in IgG levels, vaccination with live vaccines is not recommended during treatment with IMAAVY [see Warnings and Precautions (5.1)].

2.2 Recommended Dosage

Dilute IMAAVY prior to administration. Administer via intravenous infusion only [see Dosage and Administration (2.3)] .

The recommended initial dosage of IMAAVY is 30 mg/kg administered once via intravenous infusion over at least 30 minutes. Two weeks after the initial dosage administer a maintenance dosage of 15 mg/kg via intravenous infusion over at least 15 minutes. Continue the maintenance dosage every two weeks thereafter.

If a scheduled infusion appointment is missed, the maintenance dosage of IMAAVY should be administered as soon as possible. Resume dosing every two weeks thereafter.

2.3 Preparation and Administration Instructions

Prior to administration, dilute IMAAVY single-dose vials with only 0.9% sodium chloride injection using the instructions below. For patients who weigh 40 kg or more, the total volume to be administered is 250 mL; for patients who are 12 years or older and weigh less than 40 kg, the total volume to be administered is 100 mL (see Preparation) .

Preparation

Prepare the solution for infusion using aseptic technique as follows:

- Calculate the dosage (mg), total drug volume (mL) of IMAAVY solution required, and the number of IMAAVY vials needed, based on the patient's current weight [see Dosage and Administration (2.2)] . Each single-dose vial of IMAAVY is at a concentration of 185 mg/mL.
- Parenteral drug products should be inspected visually for particulate matter and discoloration prior to administration, whenever solution and container permit. Check that the solution in each vial is colorless to slightly brownish, clear to slightly opalescent, and free of visible particles. Do not use if visible particles are present or if the solution is discolored (other than colorless to slightly brownish).
- Gently withdraw the calculated volume of IMAAVY from the vial(s). Discard any unused portion of the vials.
- Dilute total volume withdrawn of IMAAVY by adding to an infusion container containing 0.9% sodium chloride injection to a final volume of:
  - 250 mL for patients who weigh 40 kg or more, or
  - 100 mL for patients who weigh less than 40 kg.
  Only use infusion containers made of polyolefin, polypropylene, or polyvinylchloride.
- Gently invert the infusion container at least 10 times to mix the solution. Do not shake.
- Verify that a uniform solution has been achieved by visual inspection. Do not use if particulate matter or discoloration is present.

Storage Conditions of the Diluted Solution

- Administer the diluted IMAAVY solution immediately after preparation.
- If the diluted IMAAVY solution is not used immediately:
  - Protect from light.
  - Store refrigerated at 2°C to 8°C (36°F to 46°F) for no more than 24 hours.
  - Do not freeze.
  - After preparation or removal from the refrigerator, use or discard the IMAAVY diluted solution within 12 hours, including infusion time. During these 12 hours, store under ambient light at 15°C to 30°C (59°F to 86°F).

Administration

- If the diluted solution is refrigerated prior to administration, allow to warm to room temperature. Do not use external heat sources to warm IMAAVY.
- Administer the diluted solution by intravenous infusion only using an infusion set with an in-line or add-on, sterile, non-pyrogenic, low protein-binding filter made of polyethersulfone or polysulfone (pore size 0.2 micrometer or less). Administration sets must be made of either polybutadiene, polyethylene, polyurethane, polypropylene, or polyvinylchloride.
- Do not infuse IMAAVY concomitantly in the same intravenous line with other agents.
- Administer IMAAVY infusion intravenously over at least 30 minutes for the initial dose (30 mg/kg) and at least 15 minutes for subsequent doses (15 mg/kg).
- If an adverse reaction occurs during administration of IMAAVY, the infusion may be slowed or stopped at the discretion of the healthcare professional.
- Monitor the patient for 30 minutes after each infusion for signs or symptoms of an infusion-related or hypersensitivity reaction [see Warnings and Precautions (5.2, 5.3)].

3 DOSAGE FORMS AND STRENGTHS

Injection: colorless to slightly brownish, clear to slightly opalescent solution available as:

- 300 mg/1.62 mL (185 mg/mL) in a single-dose vial
- 1,200 mg/6.5 mL (185 mg/mL) in a single-dose vial

4 CONTRAINDICATIONS

IMAAVY is contraindicated in patients with a history of serious hypersensitivity reaction to nipocalimab or any of the excipients in IMAAVY. Reactions have included anaphylaxis and angioedema [see Warnings and Precautions (5.2)] .

5 WARNINGS AND PRECAUTIONS

5.1 Infections

IMAAVY may increase the risk of infection [see Adverse Reactions (6.1)] . In Study 1 [see Clinical Studies (14)] , 42 (43%) out of 98 patients treated with IMAAVY reported 71 events of infection. Across Study 1 (double blind period) and its extension study (open label-period), out of 186 patients treated with IMAAVY, 132 (71%) patients reported 360 events of infection. Serious infections were reported in 7% of patients treated with IMAAVY. Delay IMAAVY administration in patients with an active infection until the infection is resolved. During treatment with IMAAVY, monitor for clinical signs and symptoms of infection. If serious infection occurs, administer appropriate treatment and consider withholding IMAAVY until the infection has resolved.

Latent Viral Infections

Patients treated with IMAAVY may be at an increased risk of activation of latent viral infections, such as herpes zoster [see Adverse Reactions (6.1)] . In the extension period of Study 1, there were 2 patients with serious adverse reactions related to Epstein-Barr virus (EBV) infection, and 1 of these patients had fatal complications. Patients who screened positive for hepatitis were excluded from Study 1. Follow standard vaccination guidelines [see Dosage and Administration (2.1)].

Immunization

The safety of immunization with live vaccines and the immune response to vaccination during treatment with IMAAVY are unknown. Because IMAAVY causes a reduction in IgG levels, vaccination with live vaccines is not recommended during treatment with IMAAVY.

Evaluate the need to administer age-appropriate vaccines according to immunization guidelines before initiation of treatment with IMAAVY.

5.2 Hypersensitivity Reactions

In clinical trials, hypersensitivity reactions, including angioedema, anaphylaxis, rash, urticaria, and eczema were observed in patients treated with IMAAVY. In Study 1, hypersensitivity reactions were mild or moderate, occurred within one hour to 2 weeks of administration [see Adverse Reactions (6.1)] . One patient experienced a hypersensitivity reaction (urticaria) that led to treatment discontinuation.

Management of hypersensitivity reactions depends on the type and severity of the reaction. Monitor the patient during treatment with IMAAVY and for 30 minutes after the administration is complete for clinical signs and symptoms of hypersensitivity reactions [see Dosage and Administration (2.3)] . If a hypersensitivity reaction occurs during administration, discontinue IMAAVY infusion and institute appropriate supportive measures if needed. IMAAVY is contraindicated in patients with a history of serious hypersensitivity to nipocalimab or any of the excipients of IMAAVY [see Contraindications (4)] .

5.3 Infusion-Related Reactions

In clinical trials, infusion-related reactions, including headache, influenza-like illness, rash, nausea, fatigue, dizziness, chills, and erythema were observed in patients treated with IMAAVY. In Study 1, infusion-related reactions were mild to moderate in severity and occurred within one hour to 2 days of administration [see Adverse Reactions (6.1)] .

Monitor patients during treatment with IMAAVY and for 30 minutes after each infusion [see Dosage and Administration (2.3)] . If a severe infusion-related reaction occurs, discontinue IMAAVY infusion and initiate appropriate therapy. Consider the risks and benefits of readministering IMAAVY following a severe infusion-related reaction. If a mild to moderate infusion related reaction occurs, patients may be rechallenged with close clinical observation, slower infusion rates, and pre-medication.

6 ADVERSE REACTIONS

The following clinically significant adverse reactions are described elsewhere in the labeling

- Infections [see Warnings and Precautions (5.1)]
- Hypersensitivity Reactions [see Warnings and Precautions (5.2)]
- Infusion-related Reactions [see Warnings and Precautions (5.3)]

6.1 Clinical Trials Experience

Because clinical trials are conducted under widely varying conditions, adverse reaction rates observed in the clinical trials of a drug cannot be directly compared to rates in the clinical trials of another drug and may not reflect the rates observed in practice.

Adults

In Study 1 and its extension study the safety of IMAAVY was evaluated in 186 patients with gMG who received at least one dose of IMAAVY. Of those patients, 168 patients were exposed to IMAAVY every 2 weeks for at least 6 months, and 140 patients were exposed for at least 12 months.

In Study 1, 98 adult patients with gMG received IMAAVY 15 mg/kg every two weeks (after 30 mg/kg initial dose) [see Clinical Studies (14)]. Of these 98 patients, approximately 67% were female, 67% were White, 29% were Asian, and 10% were of Hispanic or Latino ethnicity. The mean age at study entry was 53 years (range 20 to 81).

Adverse reactions reported in at least 5% of patients treated with IMAAVY and more frequently than placebo, are summarized in Table 1. The most common adverse reactions (reported in at least 10% of patients treated with IMAAVY) were respiratory tract infection, peripheral edema, and muscle spasms.

Table 1: Adverse Reactions (≥ 5%) of Patients Treated with IMAAVY and More Frequently than in Placebo in Study 1
Adverse Reaction | IMAAVY N=98 % | Placebo N=98 %
Infection
Respiratory tract infection [COVID-19 (and other related terms), pneumonia, bronchitis, pneumonia bacteria] | 18 | 13
Urinary tract infection [other related terms] | 6 | 3
Herpes zoster and Herpes simplex | 6 | 2
Oral infection [glossitis, oral candidiasis, pericoronitis, pulpitis dental, tooth abscess, tooth infection] | 5 | 3
Peripheral edema | 12 | 2
Muscle spasm | 12 | 3
Hypersensitivity reaction [angioedema, dermatitis atopic, eczema, gingival swelling, rash (and other related terms), urticaria] | 8 | 7
Abdominal pain | 8 | 3
Back pain | 8 | 5
Pyrexia | 7 | 1
Diarrhea | 7 | 3
Cough | 7 | 3
Anemia | 6 | 4
Dizziness | 5 | 1
Nausea | 5 | 2
Hypertension | 5 | 2
Insomnia | 5 | 2
Includes the following reported in patients treated with IMAAVY:

Infections

In Study 1 and its extension study, infections that occurred in patients treated with IMAAVY (n=186) included upper respiratory tract infection (46%), respiratory tract infection (28%; including pneumonia, bronchitis, COVID-19), urinary tract infection (15%), herpes (8%; including herpes simplex, herpes zoster, herpes zoster oticus), influenza (8%), oral infection (8%; including candidiasis and dental infections), and skin infection (7%; including cellulitis). Two (1%) cases of infections (cellulitis and urinary tract infection) led to discontinuation of IMAAVY [see Warnings and Precautions (5.1)] .

Hypersensitivity Reactions

In Study 1 and its extension study, out of 186 patients treated with IMAAVY, 30 (16%) patients experienced hypersensitivity reactions, which occurred within one hour to two weeks of administration. One patient experienced hypersensitivity reaction (urticaria) that required discontinuation of IMAAVY [see Warnings and Precautions (5.2)] .

Infusion-Related Reactions

In Study 1 and its extension study, out of 186 patients treated with IMAAVY, 20 (11%) patients experienced infusion-related reactions, which occurred within one hour to 2 days of administration. No patients experienced infusion-related reaction that required discontinuation of IMAAVY [see Warnings and Precautions (5.3)] .

Laboratory Findings

Lipids

In Study 1 (N=98), patients treated with IMAAVY had elevations from normal to high of fasting total cholesterol (≥240 mg/dL) and LDL cholesterol (≥160 mg/dL) (24% and 11% of patients, respectively). In Study 1, these changes from baseline peaked at Week 4, then decreased and plateaued by Week 24 to mean increases of 14 mg/dL and 7 mg/dL, respectively. Five percent of patients treated with IMAAVY had decreases from normal to low (<40 mg/dL of fasting HDL cholesterol).

Pediatric Patients 12 Years of Age and Older

In a 24-week, single arm study evaluating the safety of IMAAVY in 7 pediatric patients age 12 to 16 years with gMG who were AChR positive, adverse reactions were consistent with those observed in adult patients with gMG [see Use in Specific Populations (8.4)] .

7 DRUG INTERACTIONS

7.1 Effect of IMAAVY on Other Drugs

Concomitant use of IMAAVY with medications that bind to the human neonatal Fc receptor (FcRn) (e.g., immunoglobulin products, monoclonal antibodies, or antibody derivates containing the human Fc domain of the IgG subclass) may lower systemic exposures and reduce effectiveness of such medications. Closely monitor for reduced effectiveness of medications that bind to the human neonatal Fc receptor. When concomitant long-term use of such medications is essential for patient care, consider discontinuing IMAAVY, and using alternative therapies [see Clinical Pharmacology (12.3)] .

8 USE IN SPECIFIC POPULATIONS

8.1 Pregnancy

Risk Summary

There are limited data on the use of IMAAVY in pregnant women to inform a drug-associated risk of major birth defects, miscarriage, or adverse maternal or fetal outcomes.

There was no evidence of direct adverse effects on fetal development following administration of nipocalimab-aahu to pregnant monkeys; however, adverse effects on the placenta were associated with fetal loss at both doses tested (see Data) .

The background risk of major birth defects and miscarriage for the indicated population is unknown. All pregnancies have a background risk of birth defect, loss, or other adverse outcomes. In the U.S. general population, the estimated background rate of major birth defects and miscarriage in clinically recognized pregnancies is 2% to 4% and 15% to 20%, respectively.

There is a pregnancy safety study for IMAAVY. If IMAAVY is administered during pregnancy, or if a patient becomes pregnant while receiving IMAAVY, healthcare providers should report IMAAVY exposure by contacting Janssen at 1-800-526-7736 or www.IMAAVY.com

Clinical Considerations

Fetal/Neonatal Adverse Reactions

Monoclonal antibodies are increasingly transported across the placenta as pregnancy progresses, with the largest amount transferred during the third trimester. Because IMAAVY reduces maternal serum IgG concentration and impedes placental IgG transfer to the fetus, passive immunity in the infant may be reduced for 6 months or more; therefore:

- Monitor for the development of serious infection.
- Effectiveness of vaccines may be reduced.
- Consider the risks and benefits prior to administering live vaccines to infants exposed to IMAAVY in utero.

Animal Data

Intravenous administration of nipocalimab-aahu (0, 100, or 300 mg/kg) to pregnant monkeys weekly from the end of organogenesis (gestation day 45) through parturition resulted in placental ischemia, associated with fetal loss and decreased levels of IgG in the offspring at both doses tested. IgG levels in offspring returned to normal levels and no adverse effects on immune function were evident by 6 months after birth. The doses tested are 6 and 20 times the recommended human maintenance dose (15 mg/kg) on a mg/kg basis.

8.2 Lactation

Risk Summary

Nipocalimab-aahu is excreted in human colostrum and breastmilk based on limited data from an investigational study of 13 pregnant women administered nipocalimab-aahu during pregnancy where colostrum and breastmilk was assessed in the first 8 days after birth. There are insufficient data on the effect of IMAAVY in the breastfed infant. There are no data on the effect of nipocalimab on milk production. The developmental and health benefits of breastfeeding should be considered along with the mother's clinical need for IMAAVY, and any potential adverse effects on the breastfed infant from IMAAVY, or from the underlying maternal condition.

8.4 Pediatric Use

The safety and effectiveness of IMAAVY for the treatment of gMG have been established in pediatric patients 12 years of age and older. Use of IMAAVY in pediatric patients for this indication is supported by evidence from an adequate and well-controlled trial in adults with additional pharmacokinetic and safety data in pediatric patients who are 12 years of age and older [see Adverse Reactions (6.1), Clinical Pharmacology (12.3), and Clinical Studies (14)] .

Safety and effectiveness of IMAAVY for the treatment of gMG in pediatric patients below the age of 12 years have not been established.

8.5 Geriatric Use

Clinical studies of IMAAVY did not include sufficient numbers of patients aged 65 and over to determine whether they respond differently from younger adult patients.

11 DESCRIPTION

Nipocalimab-aahu, a neonatal Fc receptor blocker, is a recombinant human immunoglobulin G1 lambda (IgG1λ) monoclonal antibody, expressed in a genetically engineered Chinese hamster ovary cell line. Nipocalimab-aahu has an aglycosylated Fc region, therefore it lacks effector functions. Nipocalimab-aahu has an approximate molecular weight of 142 kilodaltons (kDa).

IMAAVY™ (nipocalimab-aahu) injection is a sterile, preservative-free, colorless to slightly brownish, clear to slightly opalescent solution, supplied in a single-dose vial for intravenous infusion after dilution.

Each single-dose vial contains either 300 mg/1.62 mL or 1,200 mg/6.5 mL of nipocalimab-aahu at a concentration of 185 mg/mL. In addition, each mL of solution contains arginine hydrochloride (25.35 mg), histidine (0.77 mg), L-histidine monohydrochloride monohydrate (1.07 mg), methionine (1.0 mg), polysorbate 80 (0.60 mg), sucrose (64.3 mg), and water for injection, USP, at a pH of 6.0.

12 CLINICAL PHARMACOLOGY

12.1 Mechanism of Action

Nipocalimab-aahu is a human IgG1 monoclonal antibody that binds to neonatal Fc receptor (FcRn), resulting in the reduction of circulating IgG levels.

12.2 Pharmacodynamics

In Study 1 [see Clinical Studies (14)], the pharmacological effect of nipocalimab-aahu was assessed by measuring the decrease in serum IgG levels and anti-AChR and anti-MuSK autoantibody levels. In patients positive for AChR and MuSK autoantibodies who were treated with IMAAVY, there was a reduction in AChR and MuSK autoantibodies relative to baseline. Decreases in total IgG levels followed a similar pattern. A similar reduction in AChR autoantibodies was observed in adolescent patients with gMG compared to adults.

12.3 Pharmacokinetics

Nipocalimab exhibits nonlinear pharmacokinetics. Following a single intravenous infusion of IMAAVY at doses ranging from 0.3 to 60 mg/kg (4 times the recommended maintenance dosage) in healthy participants, Cmax of nipocalimab-aahu increased in a dose-proportional manner while AUC increased in a greater than dose-proportional manner.

Distribution

Mean volume of distribution of nipocalimab is 2.67 L.

Metabolism

Nipocalimab is expected to be degraded by proteolytic enzymes into small peptides and amino acids.

Elimination

Nipocalimab exhibits concentration-dependent pharmacokinetics. After a single intravenous administration of 15 mg/kg nipocalimab-aahu, the mean clearance is 0.0627 L/h and half-life is 29.3 hours.

Specific Populations

Age, Sex, and Race

The pharmacokinetics of nipocalimab were not affected by age, sex, or race based on a population pharmacokinetics analysis.

Pediatric Patients

Following the recommended intravenous doses of IMAAVY in adolescent patients 12 to 16 years of age with gMG (N=7), the observed steady-state serum nipocalimab-aahu concentrations were within the range of those observed for adult patients with gMG [see Use in Specific Populations (8.4)] .

Patients with Renal Impairment

No dedicated pharmacokinetic study has been conducted in patients with renal impairment. Renal impairment is not expected to affect the pharmacokinetics of nipocalimab. Based on a population pharmacokinetic analysis, which included healthy volunteers and patients with gMG with mild to moderate renal impairment, renal function (estimated glomerular filtration rate [eGFR] 30–89 mL/min/1.73 m^2) had no clinically significant effect on nipocalimab-aahu clearance. No dose adjustment is required in patients with renal impairment.

Patients with Hepatic Impairment

No dedicated pharmacokinetic study has been performed in patients with hepatic impairment. Nipocalimab is not metabolized by cytochrome P450 enzymes, and hepatic impairment is not expected to affect the pharmacokinetics of nipocalimab. Based on a population pharmacokinetic analysis, which included healthy volunteers and patients with gMG with mild to moderate hepatic impairment, there was no clinically significant effect on nipocalimab-aahu clearance. No dose adjustment is required in patients with hepatic impairment.

Drug Interactions with Other Drugs or Biological Products

IgG-Based Monoclonal Antibodies

Nipocalimab decreases concentrations of compounds that bind to the human FcRn, including IgG based monoclonal antibodies.

Cytochrome P450 Enzymes

Nipocalimab is not metabolized by cytochrome P450 enzymes; therefore, interactions with concomitant medications that are substrates, inducers, or inhibitors of cytochrome P450 enzymes are unlikely.

12.6 Immunogenicity

The observed incidence of anti-drug antibodies is highly dependent on the sensitivity and specificity of the assay. Differences in assay methods preclude meaningful comparisons of the incidence of anti-drug antibodies in the studies described below with the incidence of anti-drug antibodies in other studies, including those of nipocalimab-aahu or of other nipocalimab products.

In clinical trials, antibodies to nipocalimab-aahu were detected in 49/102 (48%) adult and pediatric patients 12 years of age and older during 24-week treatment period.

Out of the 49 patients who were positive for antibodies to nipocalimab-aahu, 19 (38.8%) patients had neutralizing antibodies to nipocalimab-aahu. There was no identified clinically relevant effect of antibodies, including neutralizing antibodies, to nipocalimab-aahu on the pharmacokinetics, pharmacodynamics, safety, or effectiveness of IMAAVY.

13 NONCLINICAL TOXICOLOGY

13.1 Carcinogenesis, Mutagenesis, Impairment of Fertility

Carcinogenesis

Studies to assess the carcinogenic potential of nipocalimab-aahu have not been conducted.

Mutagenesis

Studies to assess the genotoxic potential of nipocalimab-aahu have not been conducted. As an antibody, nipocalimab-aahu is not expected to interact directly with DNA.

Impairment of Fertility

Once or twice weekly intravenous administration of nipocalimab-aahu (0, 20, 50, 100, or 300 mg/kg) to male and female monkeys for 26 weeks resulted in no adverse effects on reproductive organs upon histopathological examination. The highest dose tested was 20 times the recommended human maintenance dose (15 mg/kg) on a mg/kg basis.

14 CLINICAL STUDIES

The efficacy of IMAAVY for the treatment of gMG in adults who are anti-AChR or anti-MuSK antibody positive was established in a 24-week, multicenter, randomized, double-blind, placebo-controlled study (Study 1; NCT04951622). Patients were treated with IMAAVY with the recommended dosage regimen [see Dosage and Administration (2.1)] .

Study 1 enrolled patients with gMG who met the following criteria:

- Myasthenia Gravis Foundation of America (MGFA) Clinical Classification Class II to IV
- Myasthenia Gravis-Activities of Daily Living (MG-ADL) total score of at least 6
- On stable dose of standard of care MG therapy prior to baseline that included acetylcholinesterase (AChE) inhibitors, steroids or non-steroidal immunosuppressive therapies (NSISTs), either in combination or alone.

In Study 1, a total of 196 patients were randomized 1:1 to receive IMAAVY (n=98) or placebo (n=98). Baseline characteristics were similar between treatment groups. For the primary efficacy analysis population (n=153), patients had a median age of 52 years at screening (range 20 to 81 years) and a median time since diagnosis of 6 years. Sixty percent of patients were female; 63% were White; 32% were Asian; 1% were Black or African-American; and <1% were American Indian or Alaskan Native. At baseline, median MG-ADL total score was 9, and median Quantitative Myasthenia Gravis (QMG) total score was 15. Eighty-eight percent (n=134) of patients were positive for AChR antibodies and 10% (n=16) were positive for MuSK antibodies.

At baseline, in each group, 85% of patients received AChE inhibitors, 66% of patients received steroids, and 54% of patients received NSISTs at stable doses.

The efficacy of IMAAVY was measured using the MG-ADL scale, which assesses the impact of gMG on daily functions of 8 signs and symptoms that are typically affected in gMG. Each item is assessed on a 4-point scale, where a score of 0 represents normal function and a score of 3 represents loss of ability to perform that function. A total score ranges from 0 to 24, with the higher scores indicating more impairment.

The primary efficacy endpoint was the comparison of the mean change from baseline to Weeks 22, 23, and 24 between treatment groups in the MG-ADL total score. A statistically significant difference favoring IMAAVY was observed in MG-ADL total score change from baseline (p=0.002; see Table 2 and Figure 1).

The efficacy of IMAAVY was also measured using the QMG total score, which is a 13-item categorial grading system that assesses muscle weakness. Each item is assessed on a 4 -point scale, where a score of 0 represents no weakness, and a score of 3 represents severe weakness. A total possible score ranges from 0 to 39, where higher scores indicate more severe impairment.

The secondary endpoint was the comparison of the mean change from baseline to Weeks 22 and 24 between treatment groups in the QMG total score. A statistically significant difference favoring IMAAVY was observed in the QMG total score change from baseline (p<0.001; see Table 2).

The results are presented shown in Table 2.

Table 2: Least Squares Mean Change from Baseline to Week 24 in MG-ADL and QMG Total Scores in Study 1
Efficacy Endpoints | IMAAVY N = 77 LS Mean (SE) | Placebo N = 76 LS Mean (SE) | IMAAVY Change Relative to Placebo LS Mean Difference (95% CI) | p-value
Primary Endpoint
MG-ADL Total Score [Mean change from baseline over weeks 22, 23, and 24] | -4.7 (0.33) | -3.3 (0.34) | -1.5 (-2.4, -0.5) | 0.002
Secondary Endpoint
QMG Total Score [Mean change from baseline over weeks 22 and 24] | -4.9 (0.5) | -2.1 (0.5) | -2.8 (-4.2, -1.4) | <0.001
Key: CI=confidence interval; MG-ADL = Myasthenia Gravis – Activities of Daily Living; QMG = Quantitative Myasthenia Gravis; LS mean = Least squares mean; SE = standard error

Figure 1 shows the mean change from baseline to Week 24 in MG-ADL total score in Study 1, and Figure 2 shows the mean change from baseline to Week 24 in QMG total score in Study 1.

Figure 1: Least Squares Mean Change from Baseline in MG-ADL Total Score Over 24 Weeks in Study 1

LS = least squares, SE = standard error, MG-ADL = Myasthenia Gravis Activities of Daily Living

Figure 2: Least Squares Mean Change from Baseline in QMG Total Score Over 24 Weeks in Study 1

LS = least squares, SE = standard error, QMG = Quantitative Myasthenia Gravis.

16 HOW SUPPLIED/STORAGE AND HANDLING

How Supplied

IMAAVY™ (nipocalimab-aahu) injection is a sterile, preservative-free, colorless to slightly brownish, clear to slightly opalescent solution for intravenous use after dilution.

IMAAVY is supplied in cartons containing a single-dose vial per carton as:

- 300 mg/1.62 mL (185 mg/mL) | NDC 57894-800-01
- 1,200 mg/6.5 mL (185 mg/mL) | NDC 57894-801-01

Storage and Handling

Unopened Vials

Store vials refrigerated at 2°C to 8°C (36°F to 46°F) in the original carton to protect from light until the time of use. Do not freeze. Do not shake.

Diluted Solution

For storage of the diluted IMAAVY solution, see Dosage and Administration (2.3).

17 PATIENT COUNSELING INFORMATION

Advise the patient and/or caregiver to read the FDA-approved patient labeling (Patient Information).

Infections

Instruct patients to communicate any history of infections to the healthcare provider and to contact their healthcare provider if they develop any symptoms of an infection [see Warnings and Precautions (5.1)] .

Administration of Vaccines

Advise patients to complete all age-appropriate vaccines according to immunization guidelines prior to initiation of treatment with IMAAVY. Administration of live vaccines is not recommended during treatment with IMAAVY. Instruct patients to inform the healthcare provider that they are being treated with IMAAVY prior to a potential vaccination [see Warnings and Precautions (5.1)] .

Hypersensitivity Reactions

Inform patients that hypersensitivity reactions, including anaphylaxis, angioedema, rash, urticaria, and eczema have occurred in patients treated with IMAAVY. Inform patients about the signs and symptoms of hypersensitivity reactions. Advise patients to contact their healthcare provider immediately if these occur [see Warnings and Precautions (5.2)] .

Infusion-Related Reactions

Advise patients that administration of IMAAVY may result in infusion-related reactions [see Warnings and Precautions (5.3)] .

Pregnancy

Advise patients that there is a pregnancy safety study that monitors pregnancy outcomes in women exposed to IMAAVY during pregnancy, and they can be enrolled by calling 1-800-526-7736 or www.IMAAVY.com [see Use in Specific Populations (8.1)].

Manufactured by:
Janssen Biotech, Inc.
Horsham, PA 19044, USA
U.S. License No. 1864

For patent information: www.janssenpatents.com

© 2025 Janssen Pharmaceutical Companies

PATIENT INFORMATION
IMAAVY™ [im-AH-vee]
(nipocalimab-aahu)
injection, for intravenous use

What is IMAAVY?
IMAAVY is a prescription medicine used to treat adults and children 12 years of age and older with a disease called generalized myasthenia gravis (gMG) who are anti-acetylcholine receptor (AChR) or anti-muscle-specific tyrosine kinase (MuSK) antibody positive.
It is not known if IMAAVY is safe and effective in children under 12 years of age.

Do not receive IMAAVY if you:

- have a history of a severe allergic reactions to nipocalimab or any of the ingredients in IMAAVY. Reactions have included angioedema and anaphylaxis. See the end of this Patient Information leaflet for a complete list of ingredients in IMAAVY.

Before receiving IMAAVY, tell your healthcare provider about all of your medical conditions, including if you:

- ever had an allergic reaction to IMAAVY. Ask your healthcare provider if you are not sure.
- have or have had any recent infections or have any symptoms of infection.
- have recently received or are scheduled to receive an immunization (vaccine). People who are being treated with IMAAVY should not receive live vaccines.
- are pregnant or plan to become pregnant. It is not known whether IMAAVY will harm your unborn baby.
  - Pregnancy Safety Study. There is a pregnancy safety study for IMAAVY if IMAAVY is given during pregnancy or you become pregnant while receiving IMAAVY. Your healthcare provider should report IMAAVY exposure by contacting Janssen at 1-800-526-7736 or www.IMAAVY.com.
- IMAAVY can pass into your breastmilk and it is not known whether IMAAVY will harm your baby. Talk to your healthcare provider about the best way to feed your baby if you receive IMAAVY.

Tell your healthcare provider about all the medicines you take, including prescription and over-the-counter medicines, vitamins, and herbal supplements.

How will I receive IMAAVY?

- IMAAVY will be given to you by your healthcare provider through a needle placed into your vein (intravenous [IV] infusion).
- You will receive a starting dose of IMAAVY infusion lasting at least 30 minutes. Two weeks later you will receive your next dose of IMAAVY infusion lasting at least 15 minutes. Your following doses will be given every two weeks.
- If you have a reaction during your IMAAVY infusion, your healthcare provider may decide to give IMAAVY more slowly or to stop your infusion.
- If you miss a scheduled IMAAVY infusion, you should receive your next dose as soon as possible.

What should I avoid while receiving IMAAVY?

- You should not be given live vaccines while receiving IMAAVY.

What are the possible side effects of IMAAVY?
IMAAVY may cause serious side effects, including:

- Infections. Infections are a common side effect of IMAAVY that can be serious. Receiving IMAAVY may increase your risk of infection. Tell your healthcare provider right away if you have any of the following symptoms of infection:

- fever
- chills
- shivering
- cough

- sore throat
- fever blisters
- burning when you urinate

- Allergic (hypersensitivity) reactions. Allergic reactions may happen during or up to a few weeks after your IMAAVY infusion. Get emergency medical help right away if you get any of these symptoms during or after your IMAAVY infusion, which may be part of a serious allergic reaction:

- swelling of your face, lips, mouth, tongue, or throat
- difficulty swallowing or breathing

- itchy rash (hives)
- chest pain or tightness

- Infusion-related reactions. Tell your healthcare provider right away if you get any of the following symptoms during or a few days after your infusion of IMAAVY:

- headache
- rash
- nausea
- fatigue

- dizziness
- chills
- flu-like symptoms
- redness of skin

The most common side effects in people with gMG treated with IMAAVY include:

- infection in parts of your body that you use for breathing (respiratory tract infection)
- swelling in your hands, ankles, or feet (peripheral edema)
- muscle spasms

These are not all of the possible side effects of IMAAVY.
Call your doctor for medical advice about side effects. You may report side effects to FDA at 1-800-FDA-1088.

General information about the safe and effective use of IMAAVY.
Medicines are sometimes prescribed for purposes other than those listed in a Patient Information leaflet.
You can ask your pharmacist or healthcare provider for information about IMAAVY that is written for health professionals.

What are the ingredients of IMAAVY?
Active ingredient : nipocalimab-aahu
Inactive ingredients: arginine hydrochloride, histidine, L-histidine monohydrochloride monohydrate, methionine, polysorbate 80, sucrose, and water for injection.

Manufactured by: Janssen Biotech, Inc., Horsham, PA 19044, USA
U.S. License Number 1864
For patent information: www.janssenpatents.com
© 2025 Janssen Pharmaceutical Companies
For more information, call 1-800-526-7736 or go to www.IMAAVY.com

This Patient Information has been approved by the U.S. Food and Drug Administration

Issued: 4/2025

PRINCIPAL DISPLAY PANEL - 300 mg / 1.62 mL Vial Box

NDC 57894-800-01

imaavy™
(nipocalimab-aahu)
Injection

300 mg / 1.62 mL
(185 mg / mL)

For Intravenous Infusion
After Dilution

Rx only
One single-dose vial.
Discard unused portion.

Johnson
& Johnson

PRINCIPAL DISPLAY PANEL - 1,200 mg / 6.5 mL Vial Box

NDC 57894-801-01

imaavy™
(nipocalimab-aahu)
Injection

1,200 mg / 6.5 mL
(185 mg / mL)

For Intravenous Infusion
After Dilution

Rx only
One single-dose vial.
Discard unused portion.

Johnson
& Johnson